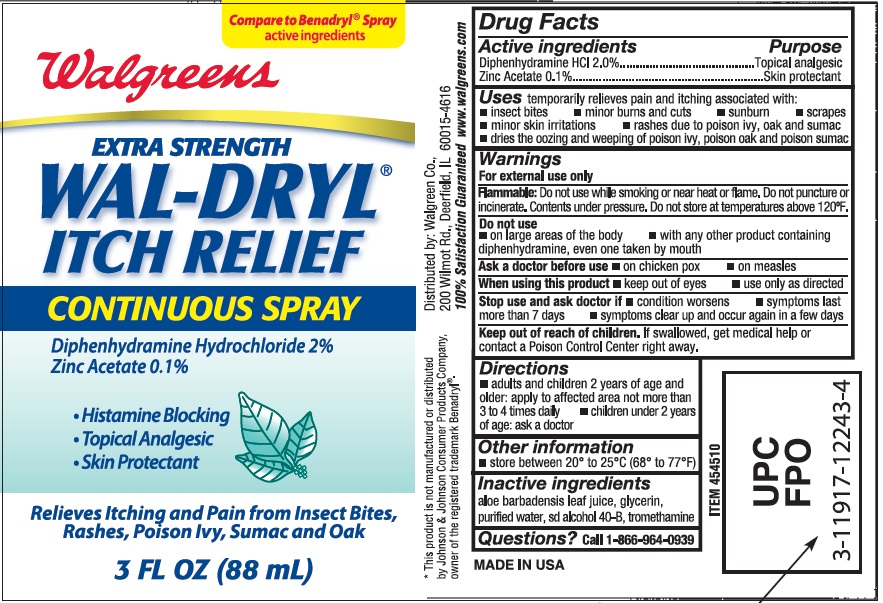 DRUG LABEL: EXTRA STRENGTH WAL-DRYL ITCH RELIEF
NDC: 0363-2177 | Form: SPRAY
Manufacturer: WALGREEN CO
Category: otc | Type: HUMAN OTC DRUG LABEL
Date: 20231227

ACTIVE INGREDIENTS: DIPHENHYDRAMINE HYDROCHLORIDE 20 mg/1 mL; ZINC ACETATE 1 mg/1 mL
INACTIVE INGREDIENTS: ALOE VERA LEAF; GLYCERIN; WATER; ALCOHOL; TROMETHAMINE

WALGREENS EXTRA STRENGTH WAL-DRYL ITCH RELIEF CONTINUOUS SPRAY

Active Ingredients:

Diphenhydramine HCL 2.0% Topical Analgesic

Zinc Acetate 0.1% Skin Protectant

Purpose

Topical Analgesic, Skin protectant.

Uses:

Temporarily relieves pain and itching associated with:

insect bites, minor burns and cuts, sunburn, scrapes, minor skin irritations, rashes due to poison ivy, oak and sumac, dries the oozing and weeping of poison ivy, poison oak and poison sumac.

Warnings:

For external use only.

flammable: do not use while smokingo r near heat or flame. Do not puncture or incinerate. Contents under pressure. Do not store at temperatures above 120degrees F.

Do not use

On large areas of the body.
with any other product containing diphenhydramine, even one taken by mouth.

Ask a doctor before use

on chicken pox

on measles

When using this product, keep out of eyes, use only as directed.

Stop use and ask doctor if:

condition worsens

symptoms last more than 7 days

symptoms clear up and occur again in a few days.

Keep out of reach of children. If swallowed, get medical help or contact a Poison Control Center right away.

Directions

Adults and children 2 years of age and older: apply to affected area not more than 3 to 4 times daily

children under 2 years of age: ask a doctor.

Other Information

store between 20 and 25 degrees C (68 to 77 degrees F)

Inactive Ingredients

Aloe barbadensis leaf juice, glycerin, purified water, sd alcohol 40-B, tromethamine

QUESTIONS

Call 1-866-964-0939

DESCRIPTION

*This product is not manufactured or distributed by Johnson and Johnson consumer Products company, owner of the Registered trademark Benadryl

Distributed by Walgreen Co.

200 Wilmot Rd., Deerfield, IL 60015-4616

100% Satisfaction Guaranteed www.walgreens.com

MADE IN USA

PACKAGE LABEL

Compare to Benadryl(r) Spray

Active ingredients

Walgreens

Extra Strength

Wal-Dryl

Itch Relief

Continuous Spray

Diphenhydramine Hydrochloride 2%

Zinc Acetate 0.1%

Histamine Blocking

Topical Analgesic

Skin Protectant

Relieves itching and pain from insect bites, rashes, poison ivy, sumac and oak.

3 fl oz (88mL)